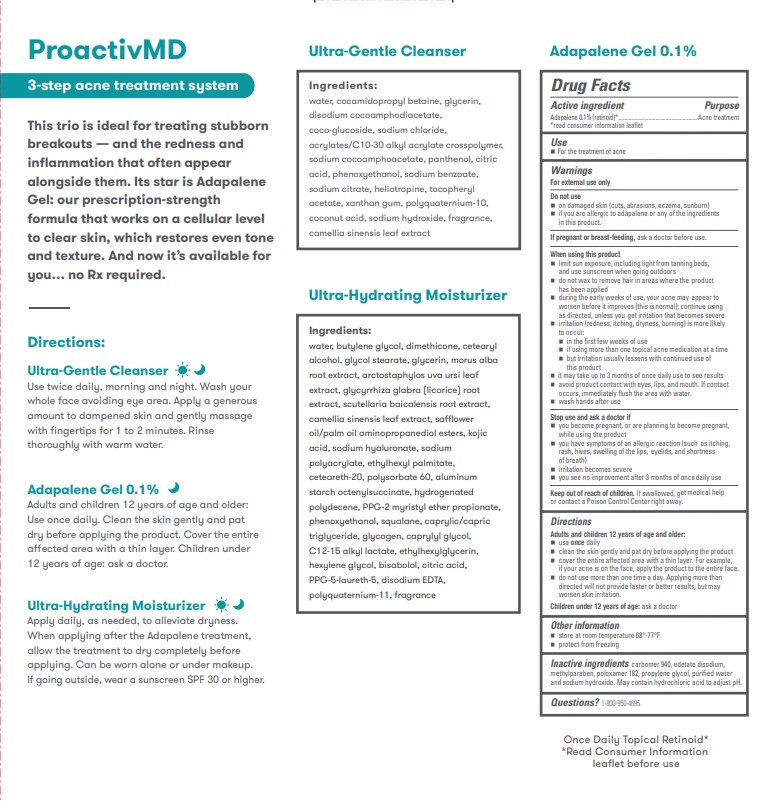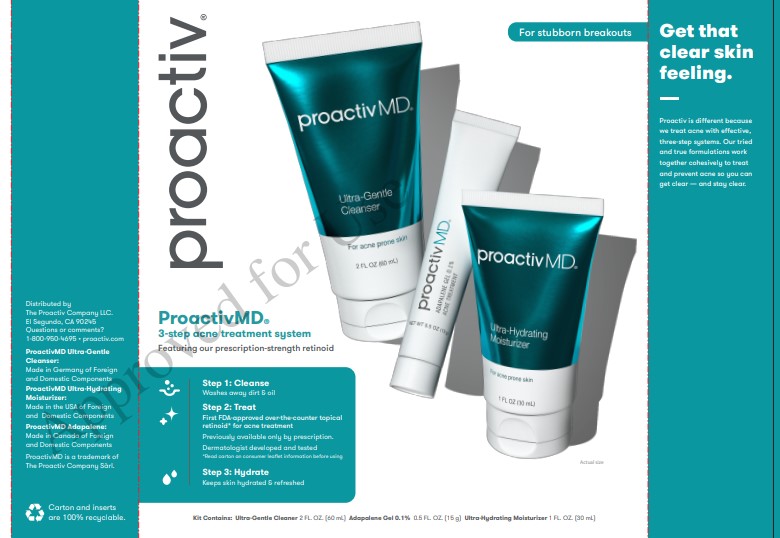 DRUG LABEL: Proactiv MD Kit
NDC: 11410-224 | Form: KIT | Route: TOPICAL
Manufacturer: Alchemee, LLC
Category: otc | Type: HUMAN OTC DRUG LABEL
Date: 20260107

ACTIVE INGREDIENTS: ADAPALENE 0.1 g/100 g
INACTIVE INGREDIENTS: SODIUM HYDROXIDE; PROPYLENE GLYCOL; PHENOXYETHANOL; CARBOMER HOMOPOLYMER TYPE C (ALLYL PENTAERYTHRITOL CROSSLINKED); WATER; EDETATE DISODIUM; POLOXAMER 182

Proactiv MD Kit

Adapalene Gel 0.1% - Drug Facts

Drug Facts

Adapalene Gel 0.1% - Active ingredient

Adapalene Gel 0.1% (retinoid)

Adapalene Gel 0.1% - Purpose

Acne treatment

Adapalene Gel 0.1% - Use

for the treatment of acne

Adapalene Gel 0.1% - Warnings

For external use only

Do not use

- on damaged skin (cuts, abrasions, eczema, sunburn)
- if you're allergic to adapalene or any of the ingredients in this product

Adapalene Gel 0.1% - When using this product

- limit sun exposure, including light from tanning beds, and use sunscreen when going outdoors
- do not wax to remove hair in areas where the product has been applied
- during the early weeks of use, your acne may appear to worsen before it improves (this is normal); continue using as directed, unless you get irritation that becomes severe
  - irritation (redness, itching, dryness, burning) is more likely to occur:
    - in the first few weeks of use
    - if using more than one topical acne medication at a time
    - but irritation usually lessens with continued use of this product
    - it may take up to 3 months of once daily use to see results
    - avoid product contact with eyes, lips, and mouth. If contact occurs, immediately flush the area with water.
    - wash hands after use

Stop use and ask a doctor if

- irritation becomes severe.

Keep out of reach of children.If swallowed, get medical help or contact a Poison Control Center right away.

Adapalene Gel 0.1% - Keep out of reach of children

If swallowed, get medical help or contact a Poison Control Center right away.

Adapalene Gel 0.1% - Directions

Adults and children 12 years of age and older:

- use once daily
- clean the skin gently and pat dry before applying the product
- cover the entire affected area with a thin layer. For example, if your acne is on the face, apply the product to the entire face.
- do not use more than one time a day. Applying more than directed will not provide faster or better results, but may worsen skin irritation.

Children under 12 years of age: ask a doctor

Adapalene Gel 0.1% - Other information

- Store at room temperature 68o – 77oF
- protect from freezing

Adapalene Gel 0.1% - Inactive ingredients

carbomer, disodium EDTA, phenoxyethanol, poloxamer 182, propylene glycol, sodium hydroxide, water

Questions or comments?

1-800-950-4695

Distributed by Alchemee LLC
Santa Monica, CA 90401
Made in the USA of Foreign
and Domestic Components
Questions? 1-800-950-4695 • proactiv.com
Proactiv is a registered trademark
of Taro Pharmaceuticals U.S.A., Inc.

PRINCIPAL DISPLAY PANEL - ProactivMD Kit

proactiv®

ProactivMD

3-step acne treatment system

Featuring our prescription-strength retinoid

Step 1: Cleanse

Washes away debris & oil

Step 2: Treat

First FDA-approved over-the-counter topical retinoid* for acne treatment
Previously available only by prescription.
Dermatologist developed and tested
*Read carton an consumer leaflet information before using
Step 3: Hydrate
Keeps skin hydrated & refreshed

Kit Contains: Ultra-Gentle Cleaner 2 FL. OZ. (60 mL) Adapalene Gel 0.1% 0.5 FL. OZ. (15 g) Ultra-Hydrating Moisturizer 1 FL. OZ. (30 mL)